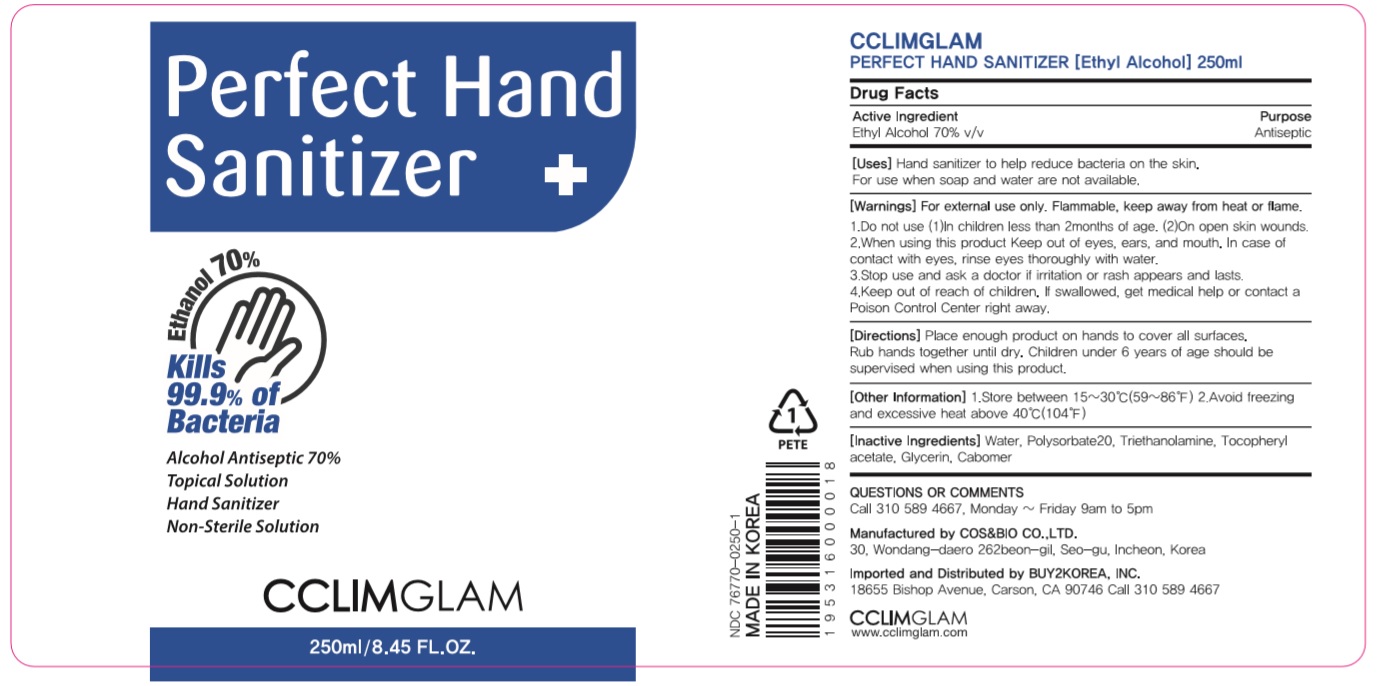 DRUG LABEL: CCLIMGLAM PERFECT HAND SANITIZER (Ethyl Alcohol)
NDC: 76770-0250 | Form: GEL
Manufacturer: COS&BIO Co Ltd
Category: otc | Type: HUMAN OTC DRUG LABEL
Date: 20200527

ACTIVE INGREDIENTS: ALCOHOL 175 mL/250 mL
INACTIVE INGREDIENTS: ALPHA-TOCOPHEROL ACETATE; GLYCERIN; CARBOMER HOMOPOLYMER, UNSPECIFIED TYPE; WATER; TROLAMINE; POLYSORBATE 20

[COS&BIO Co Ltd] CCLIMGLAM PERFECT HAND SANITIZER (Ethyl Alcohol)
250 ml Bottle+Pump
76770-0250-1